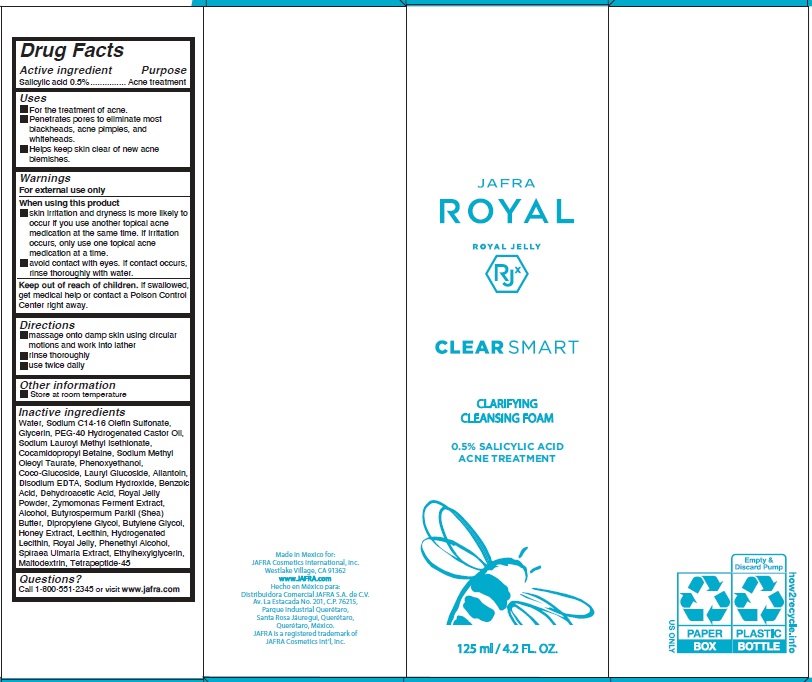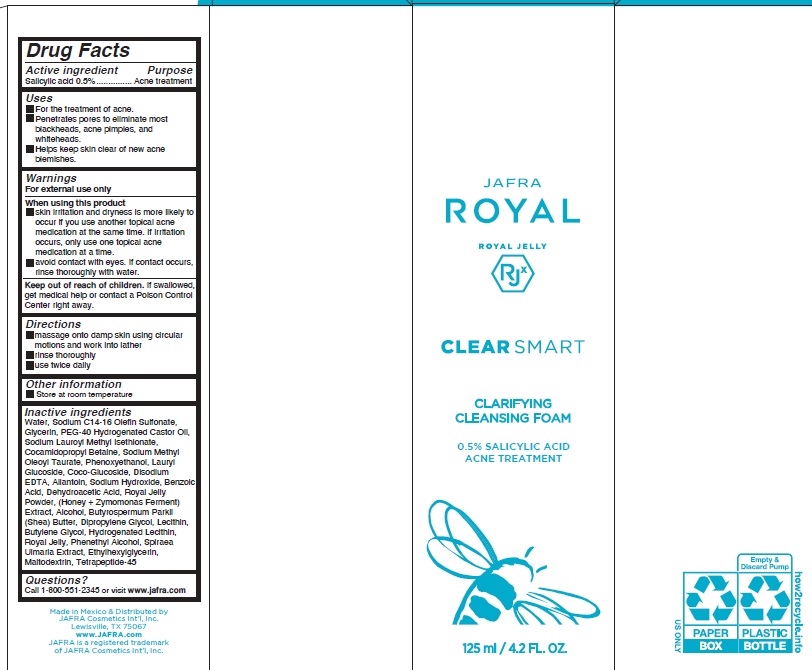 DRUG LABEL: Clear Smart Clarifying Cleansing Foam
NDC: 68828-244 | Form: LIQUID
Manufacturer: Distribuidora Comercial Jafra, S.A. de C.V.
Category: otc | Type: HUMAN OTC DRUG LABEL
Date: 20251021

ACTIVE INGREDIENTS: SALICYLIC ACID 0.5 g/100 mL
INACTIVE INGREDIENTS: DIPROPYLENE GLYCOL; WATER; ALLANTOIN; SHEA BUTTER; GLYCERIN; LAURYL GLUCOSIDE; MALTODEXTRIN; POLYOXYL 40 HYDROGENATED CASTOR OIL; COCO GLUCOSIDE; EDETATE DISODIUM; ROYAL JELLY; SODIUM HYDROXIDE; SODIUM LAUROYL METHYL ISETHIONATE; BENZOIC ACID; COCAMIDOPROPYL BETAINE; ALCOHOL; PHENOXYETHANOL; ETHYLHEXYLGLYCERIN; HONEY; HYDROGENATED SOYBEAN LECITHIN; PHENYLETHYL ALCOHOL; SODIUM C14-16 OLEFIN SULFONATE; LECITHIN, SOYBEAN; SODIUM METHYL OLEOYL TAURATE; BUTYLENE GLYCOL; DEHYDROACETIC ACID; FILIPENDULA ULMARIA ROOT

Clear Smart Clarifying Cleansing Foam

Active ingredient

Salicylic Acid 0.5%

Purpose

Acne treatment

Uses

- For the treatment of acne.
- Penetrates pores to eliminate most blackheads, acne pimples, and whiteheads.
- Helps keep skin clear of new acne blemishes.

Warnings

For external use only

When using this product

- skin irritation and dryness is more likely to occur if you use another topical acne medication at the same time. If irritation occurs, only use one topical acne medication at a time.
- avoid contact with eyes. If contact occurs, rinse thoroughly with water.

Keep out of reach of children.If swallowed, get medical help or contact a Poison Control Center right away.

Directions

- massage onto damp skin using circular motions and work into lather
- rinse thoroughly
- use twice daily

Other information

- Store at room temperature

Inactive Ingredients

Water, Sodium C14-16 Olefin Sulfonate, Glycerin, PEG-40 Hydrogenated Castor Oil, Sodium Lauroyl Methyl Isethionate, Cocamidopropyl Betaine, Sodium Methyl Oleoyl Taurate, Phenoxyethanol, Lauryl Glucoside, Coco-Glucoside, Disodium EDTA, Allantoin, Sodium Hydroxide, Benzoic Acid, Dehydroacetic Acid, Royal Jelly Powder, (Honey + Zymomonas Ferment) Extract, Alcohol, Butyrospermum Parkii (Shea) Butter, Dipropylene Glycol, Lecithin, Butylene Glycol, Hydrogenated Lecithin, Royal Jelly, Phenethyl Alcohol, Spiraea Ulmaria Extract, Ethylhexylglycerin, Maltodextrin, Tetrapeptide-45

Questions?Call 1-800-551-2345 or visit www.jafra.com